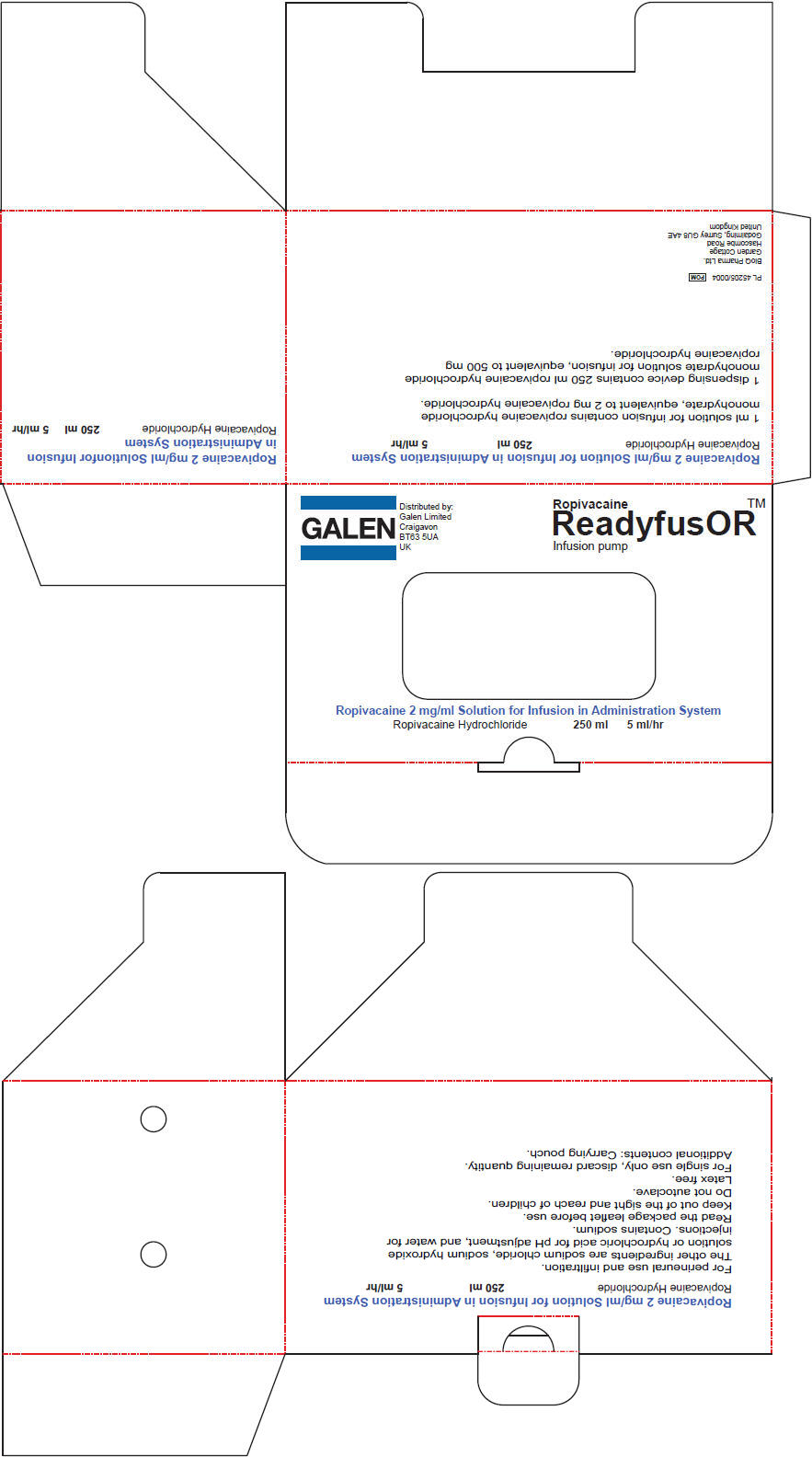 DRUG LABEL: ReadyfusOR Ropivacaine
NDC: 71807-011 | Form: INJECTION, SOLUTION
Manufacturer: BioQ Pharma Incorporated
Category: prescription | Type: HUMAN PRESCRIPTION DRUG LABEL
Date: 20180622

ACTIVE INGREDIENTS: ROPIVACAINE HYDROCHLORIDE ANHYDROUS 2 mg/1 mL
INACTIVE INGREDIENTS: SODIUM CHLORIDE; WATER; HYDROCHLORIC ACID; SODIUM HYDROXIDE

Ropivacaine

PRINCIPAL DISPLAY PANEL - 250 mL Bottle Carton

GALEN
Distributed by:
Galen Limited
Craigavon
BT63 5UA
UK

Ropivacaine
ReadyfusOR™
Infusion pump

Ropivacaine 2 mg/ml Solution for Infusion in Administration System

Ropivacaine Hydrochloride
250 ml
5 ml/hr